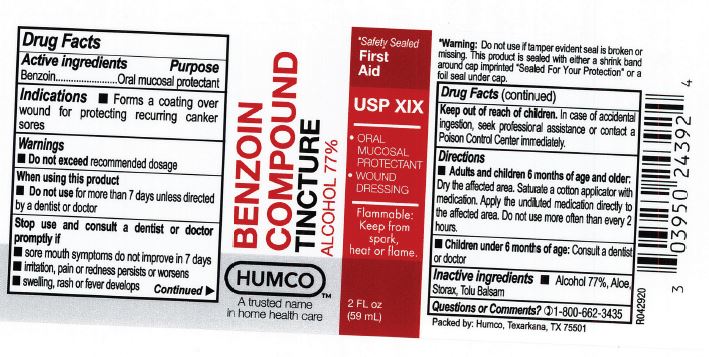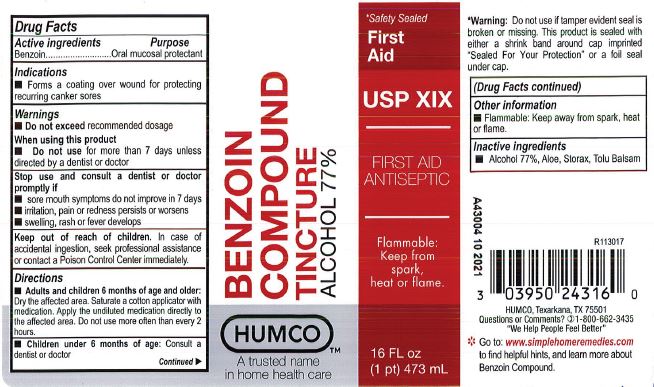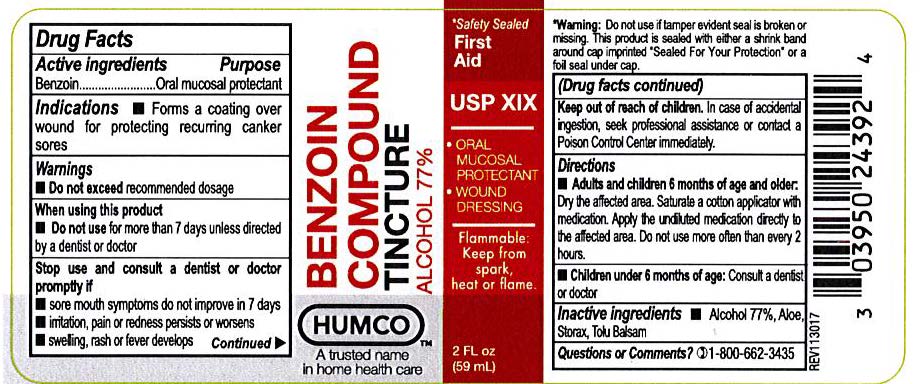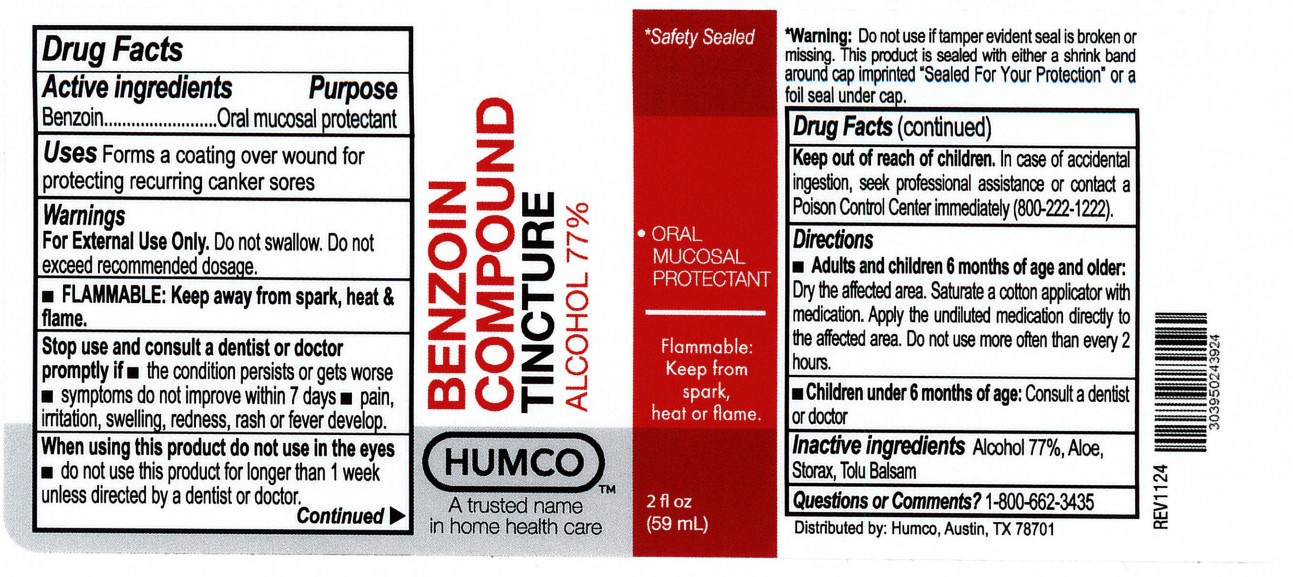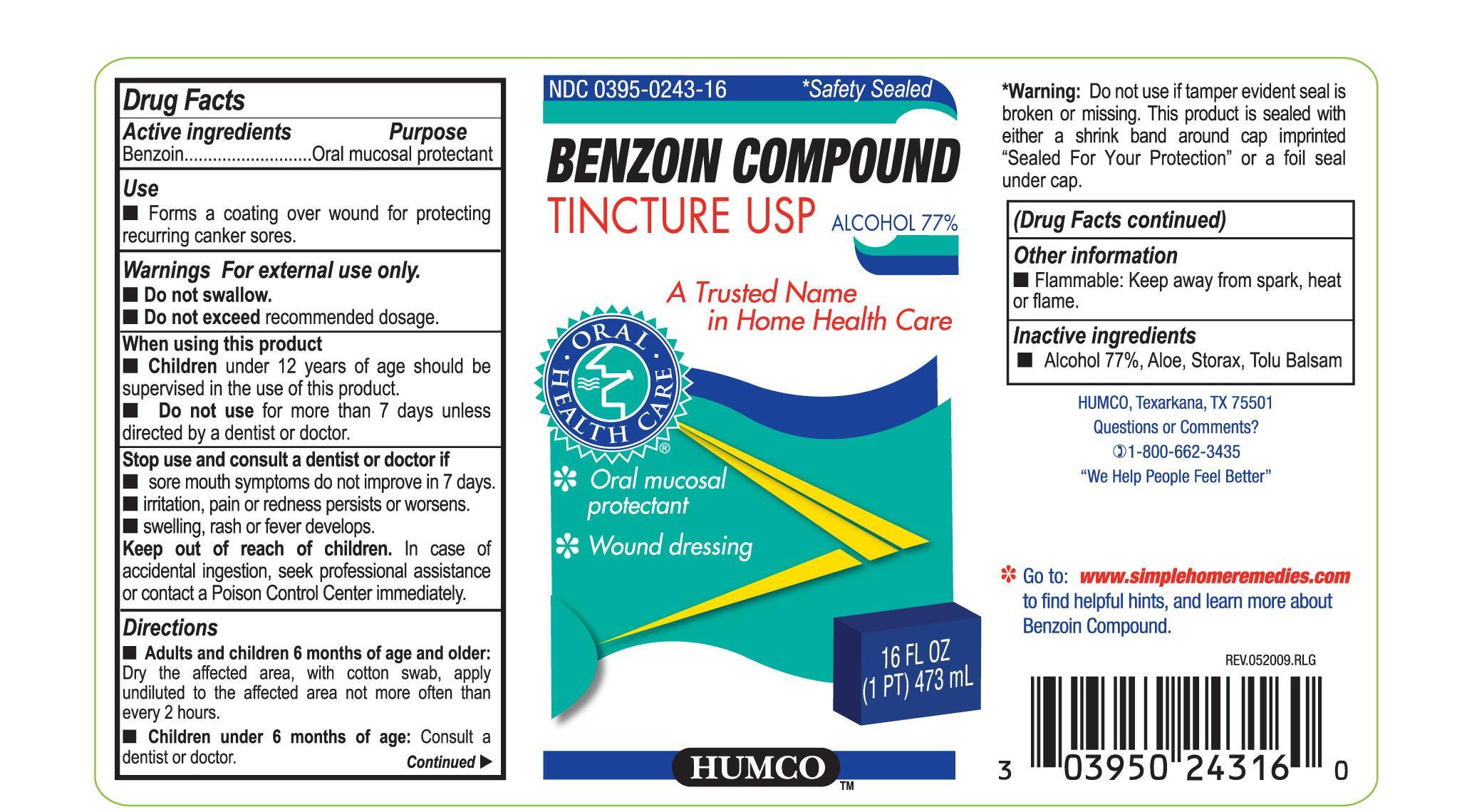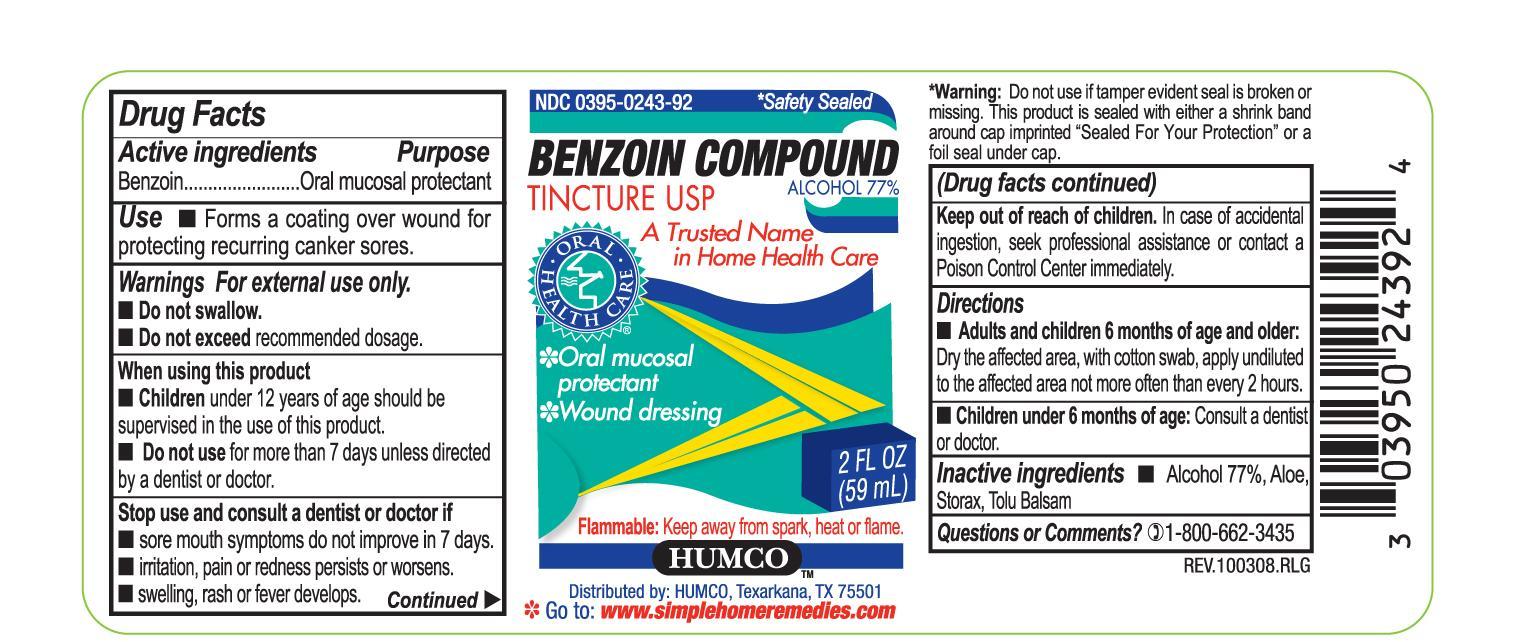 DRUG LABEL: Benzoin Compound Tincture
NDC: 0395-0243 | Form: LIQUID
Manufacturer: Humco Holding Group, Inc.
Category: otc | Type: HUMAN OTC DRUG LABEL
Date: 20251211

ACTIVE INGREDIENTS: BENZOIN RESIN 1000 mg/1 mL
INACTIVE INGREDIENTS: ALCOHOL; ALOE; TOLU BALSAM

Humco Benzoin Compound Tincture, USP

Drug Facts

Active Ingredient

Benzoin

Purpose

Oral mucosal protectant

Use

Forms a coating over wound for protecting recurring canker sores

Warnings

For external use only. Do not swallow. Do not exceed recommended dosage.

When using this product

Children under 12 years of age should be supervised in the use of this product.

Do not use for more than 7 days unless directed by a dentist or doctor.

Stop use and consult a dentist or doctor if

sore mouth symptoms do not improve in 7 days. irritation, pain or redness persists or worsens. swelling, rash or fever develops.

Keep out of reach of children.

In case of accidental ingestion, seek professional assistance or contact a Poison Control Center immediately.

Directions

Adults and children 6 months of age and older: Dry the affected area, with cotton swab, apply undiluted to the affected area not more often than every 2 hours.

Children under 6 months of age: Consult a dentist or doctor.

Other information

Flammable: Keep away from spark, heat or flame.

Inactive Ingredients

Alcohol 77%, Aloe, Storax, Tolu Balsam